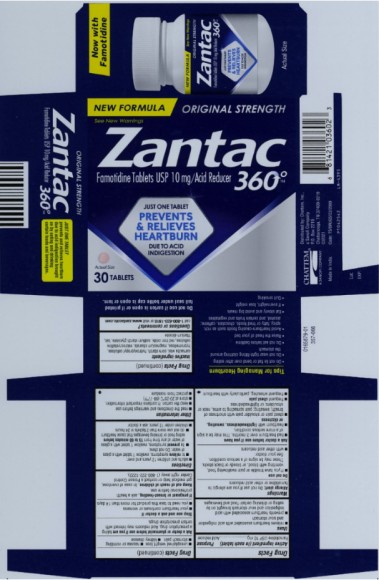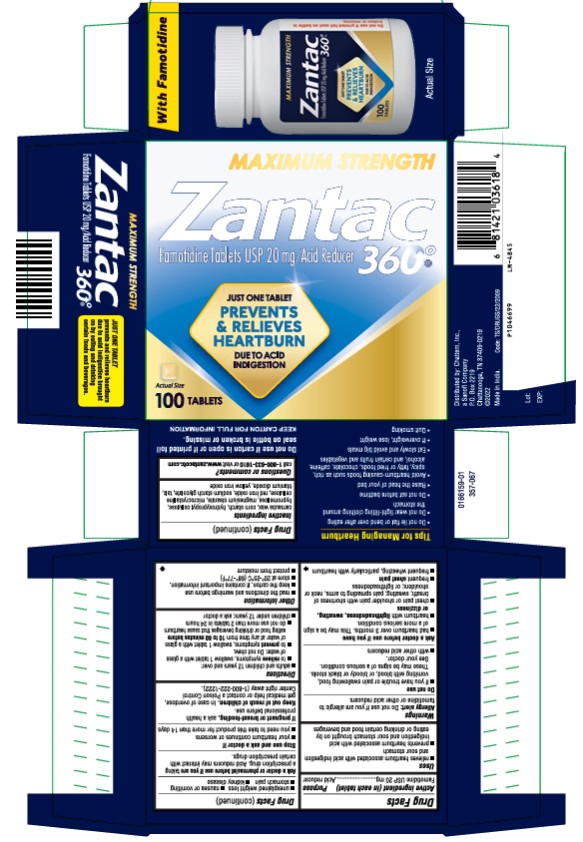 DRUG LABEL: Zantac 360
NDC: 41167-0360 | Form: TABLET, FILM COATED
Manufacturer: Chattem, Inc.
Category: otc | Type: HUMAN OTC DRUG LABEL
Date: 20250509

ACTIVE INGREDIENTS: FAMOTIDINE 10 mg/1 1
INACTIVE INGREDIENTS: CARNAUBA WAX; STARCH, CORN; HYDROXYPROPYL CELLULOSE (1600000 WAMW); HYPROMELLOSE 2910 (5 MPA.S); MAGNESIUM STEARATE; MICROCRYSTALLINE CELLULOSE; FERRIC OXIDE RED; SODIUM STARCH GLYCOLATE TYPE A CORN; TALC; TITANIUM DIOXIDE

Zantac 360

Zantac 360⁰

Famotidine Tablets 10 mg / Acid Reducer

Drug Facts

Active ingredient (in each tablet)

Famotidine USP 10 mg

Purpose

Acid reducer

Uses

■ relieves heartburn associated with acid indigestion and sour stomach

■ prevents heartburn associated with acid indigestion and sour stomach brought on by eating or drinking certain food and beverages

Warnings

Allergy alert: Do not use if you are allergic to famotidine or other acid reducers

Do not use

■ if you have trouble or pain swallowing food, vomiting with blood, or bloody or black stools. These may be signs of a serious condition. See your doctor.

■ with other acid reducers

Ask a doctor before use if you have

■ had heartburn over 3 months. This may be a sign of a more serious condition.

■ heartburn with lightheadedness, sweating or dizziness

■ chest pain or shoulder pain with shortness of breath; sweating; pain spreading to arms, neck or shoulders; or lightheadedness

■ frequent chest pain

■ frequent wheezing, particularly with heartburn

■ unexplained weight loss

■ nausea or vomiting

■ stomach pain

■ kidney disease

Ask a doctor or pharmacist before use if you are

taking a prescription drug. Acid reducers may interact with certain prescription drugs.

Stop use and ask a doctor if

■ your heartburn continues or worsens

■ you need to take this product for more than 14 days

If pregnant or breast-feeding,

ask a health professional before use.

Keep out of reach of children.

In case of overdose, get medical help or contact a Poison Control Center right away. (1-800-222-1222)

Directions

■ adults and children 12 years and over:

■ to relieve symptoms, swallow 1 tablet with a glass of water. Do not chew.

■ to prevent symptoms, swallow 1 tablet with a glass of water at any time from 15 to 60 minutes before eating food or drinking beverages that cause heartburn

■ do not use more than 2 tablets in 24 hours

■ children under 12 years: ask a doctor

Other information

■ read the directions and warnings before use

■ keep the carton. It contains important information.

■ store at 20-25°C (68-77°F)

■ protect from moisture

Inactive ingredients

carnauba wax, corn starch, hydroxypropyl cellulose, hypromellose, magnesium stearate, microcrystalline cellulose, red iron oxide, sodium starch glycolate, talc, titanium dioxide

Questions or comments

call 1-800-633-1610 or visit www.zantacotc.com

Tips for Managing Heartburn

■ Do not lie flat or bend over after eating

■ Do not wear tight-fitting clothing around the stomach

■ Do not eat before bedtime

■ Raise the head of your bed

■ Avoid heartburn-causing foods such as rich, spicy, fatty or fried foods, chocolate, caffeine, alcohol, and certain fruits and vegetables

■ Eat slowly and avoid big meals

■ If overweight, lose weight

■ Quit smoking

Zantac 360⁰

Famotidine Tablets 20 mg / Acid Reducer

Drug Facts

Active ingredient (in each tablet)

Famotidine USP 20 mg

Purpose

Acid reducer

Uses

■ relieves heartburn associated with acid indigestion and sour stomach

■ prevents heartburn associated with acid indigestion and sour stomach brought on by eating or drinking certain food and beverages

Warnings

Allergy alert: Do not use if you are allergic to famotidine or other acid reducers

Do not use

■ if you have trouble or pain swallowing food, vomiting with blood, or bloody or black stools. These may be signs of a serious condition. See your doctor.

■ with other acid reducers

Ask a doctor before use if you have

■ had heartburn over 3 months. This may be a sign of a more serious condition.

■ heartburn with lightheadedness, sweating or dizziness

■ chest pain or shoulder pain with shortness of breath; sweating; pain spreading to arms, neck or shoulders; or lightheadedness

■ frequent chest pain

■ frequent wheezing, particularly with heartburn

■ unexplained weight loss

■ nausea or vomiting

■ stomach pain

■ kidney disease

Ask a doctor or pharmacist before use if you are

taking a prescription drug. Acid reducers may interact with certain prescription drugs.

Stop use and ask a doctor if

■ your heartburn continues or worsens

■ you need to take this product for more than 14 days

If pregnant or breast-feeding,

ask a health professional before use.

Keep out of reach of children.

In case of overdose, get medical help or contact a Poison Control Center right away. (1-800-222-1222)

Directions

■ adults and children 12 years and over:

■ to relieve symptoms, swallow 1 tablet with a glass of water. Do not chew.

■ to prevent symptoms, swallow 1 tablet with a glass of water at any time from 10 to 60 minutes before eating food or drinking beverages that cause heartburn

■ do not use more than 2 tablets in 24 hours

■ children under 12 years: ask a doctor

Other information

■ read the directions and warnings before use

■ keep the carton. It contains important information.

■ store at 20-25°C (68-77°F)

■ protect from moisture

Inactive ingredients

carnauba wax, corn starch, hydroxypropyl cellulose, hypromellose, magnesium stearate, microcrystalline cellulose, red iron oxide, sodium starch glycolate, talc, titanium dioxide, yellow iron oxide

Questions or comments?

call 1-800-633-1610 or visit www.zantacotc.com

Tips for Managing Heartburn

■ Do not lie flat or bend over after eating

■ Do not wear tight-fitting clothing around the stomach

■ Do not eat before bedtime

■ Raise the head of your bed

■ Avoid heartburn-causing foods such as rich, spicy, fatty or fried foods, chocolate, caffeine, alcohol, and certain fruits and vegetables

■ Eat slowly and avoid big meals

■ If overweight, lose weight

■ Quit smoking

PRINCIPAL DISPLAY PANEL

Zantac
Famotidine Tablets USP 10 mg / Acid Reducer
360
30 Tablets

PRINCIPAL DISPLAY PANEL

MAXIMUM STRENGTH
Zantac
Famotidine Tablets USP 20 mg/Acid Reducer
360
100 TABLETS